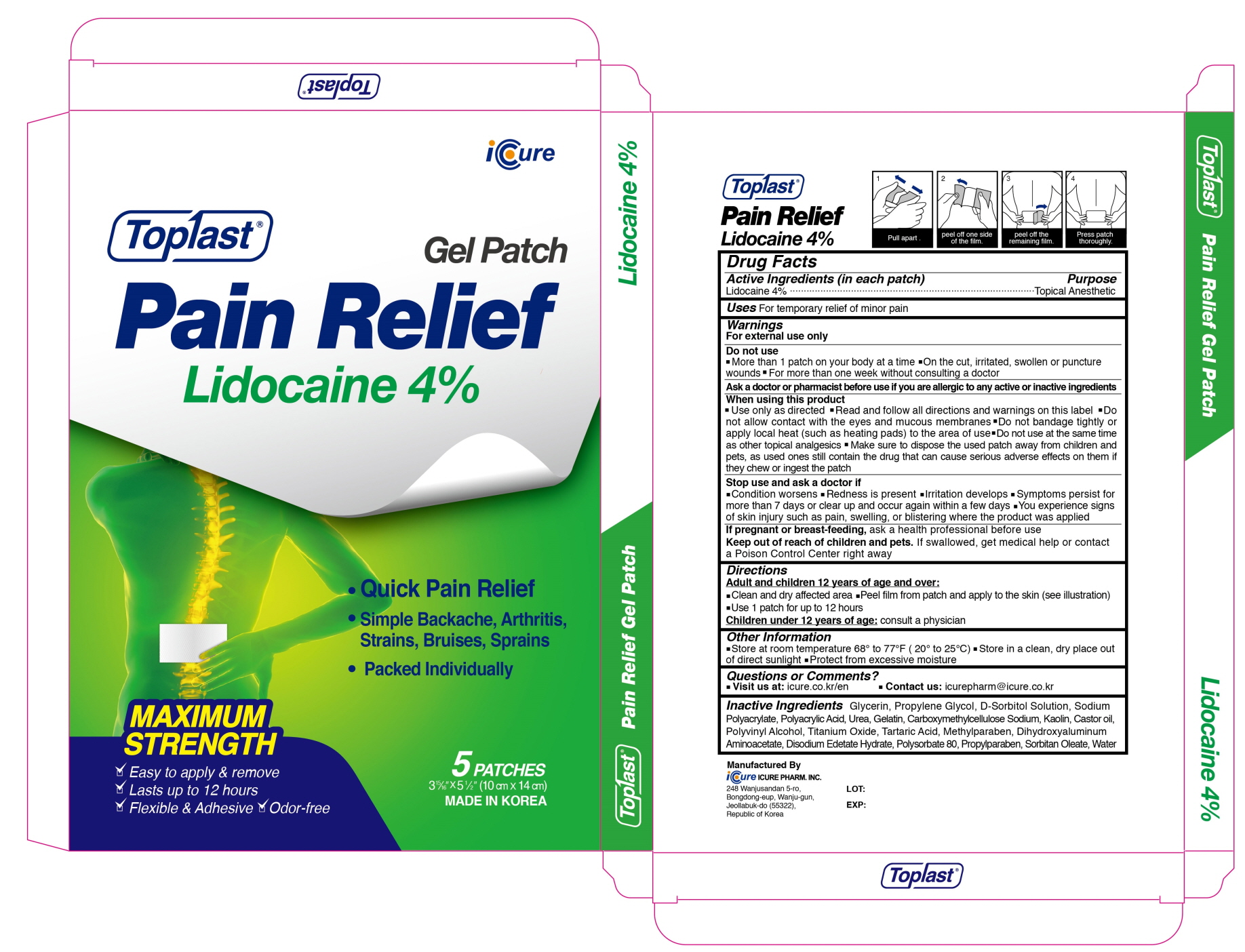 DRUG LABEL: Toplast Pain Relief Lidocaine 4percent
NDC: 73279-0005 | Form: PATCH
Manufacturer: Icure Pharmaceutical Inc, Wanju Factory
Category: otc | Type: HUMAN OTC DRUG LABEL
Date: 20200716

ACTIVE INGREDIENTS: Lidocaine 240 mg/1 1
INACTIVE INGREDIENTS: Glycerin; Propylene Glycol; SORBITOL; Urea; CARBOXYMETHYLCELLULOSE SODIUM, UNSPECIFIED; Gelatin; Kaolin; POLYVINYL ALCOHOL, UNSPECIFIED; TITANIUM DIOXIDE; Tartaric Acid; Methylparaben; Dihydroxyaluminum Aminoacetate; EDETATE DISODIUM; Polysorbate 80; Propylparaben; SORBITAN MONOOLEATE; Water

Drug Facts

ACTIVE INGREDIENTS

Lidocaine 4%

INACTIVE INGREDIENTS

Glycerin, Propylene Glycol, D-Sorbitol Solution, Sodium Polyacrylate, Polyacrylic Acid, Urea, Gelatin, Carboxymethylcellulose Sodium, Kaolin, Castor Oil, Polyvinyl Alcohol, Titanium Oxide, Tartaric Acid, Methylparaben, Dihydroxyaluminum Aminoacetate, Disodium Edetate Hydrate, Polysorbate 80, Propylparaben, Sorbitan Oleate, Water

PURPOSE

Topical Anesthetic

WARNINGS

For external use only
--------------------------------------------------------------------------------------------------------
Do not use
■ More than 1 patch on your body at a time ■ On the cut, irritated, swollen or puncture wounds ■ For more than one week without consulting a doctor
--------------------------------------------------------------------------------------------------------
Ask a doctor or pharmacist before use if you are allergic to any active or inactive ingredients
--------------------------------------------------------------------------------------------------------
When using this product
■ Use only as directed ■ Read and follow all directions and warnings on this label ■ Do not allow contact with the eyes and mucous membranes ■ Do not bandage tightly or apply local heat (such as heating pads) to the area of use ■ Do not use at the same time as other topical analgesics ■ Make sure to dispose the used patch away from children and pets, as used ones still contain the drug that can cause serious adverse effects on them if they chew or ingest the patch
--------------------------------------------------------------------------------------------------------
Stop use and ask a doctor if
■ Condition worsens ■ Redness is present ■ Irritation develops ■ Symptoms persist for more than 7 days or clear up and occur again within a few days ■ You experience signs of skin injury such as pain, swelling or blistering where the product was applied
--------------------------------------------------------------------------------------------------------
If pregnant or breast-feeding, ask a health professional before use

Keep out of reach of children and pets

If swallowed, get medical help or contact a Poison Control Center right away

Uses

For temporary relief of minor pain

Directions

Adult and children 12 years of age and over :
■ Clean and dry affected area ■ Peel film from patch and apply to the skin (see illustration) ■ Use 1 patch for up to 12 hours
Children under 12 years of age : Consult a physician

Other Information

■ Store at room temperature 68° to 77°F (20° to 25°C) ■ Store in a clean, dry place out of direct sunlight ■ Protect from excessive moisture

Questions or Comments

■ Visit us at : icure.co.kr/en ■ Contact us : icurepharm@icure.co.kr